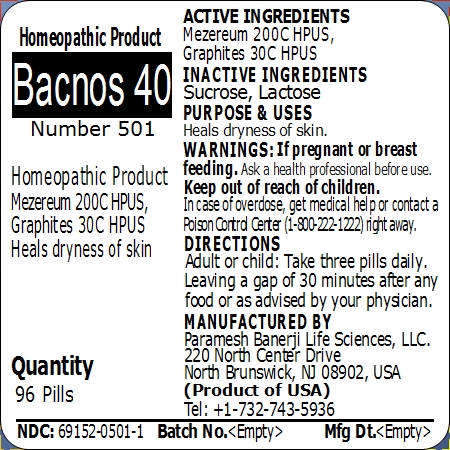 DRUG LABEL: Bacnos 40 (Number 501)
NDC: 69152-0501 | Form: PELLET
Manufacturer: Paramesh Banerji Life Sciences LLC
Category: homeopathic | Type: HUMAN OTC DRUG LABEL
Date: 20150209

ACTIVE INGREDIENTS: GRAPHITE 30 [hp_C]/1 1; DAPHNE MEZEREUM BARK 200 [hp_C]/1 1
INACTIVE INGREDIENTS: LACTOSE; SUCROSE

Active Ingredients

Mezereum 200C HPUS, Graphites 30C HPUS

Inactive Ingredients

Sucrose, Lactose

Purpose

Heals dryness of skin

Uses

Heals dryness of skin

Warnings

If pregnant or breast feeding ask a health professional before use.

Keep out of reach of children. In case of overdose, get medical help or contact a Poison Control Center (1-800-222-1222) right away.

Direction

Adult or child: Take three pills daily. Leaving a gap of 30 minutes after any food or as advised by your physician.

Manufactured by

Paramesh Banerji Life Sciences, LLC

220 North Center Drive

North Brunswick, NJ 08902, USA

Product of USA

Tel: +1-732-743-5936

Principal Display Panel

Homeopathic Product

Bacnos 40

Number 501

Homeopathic Product

Mezereum 200C HPUS, Graphites 30C HPUS

Heals dryness of skin

Quantity

96 Pills